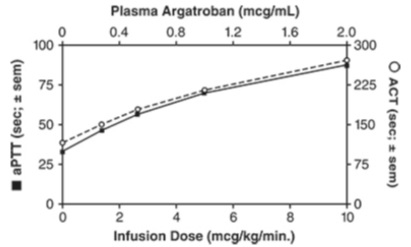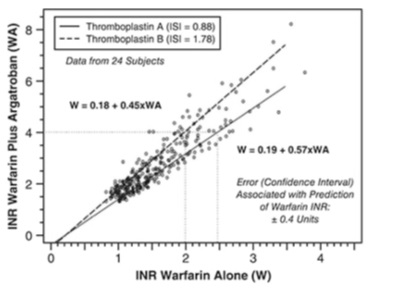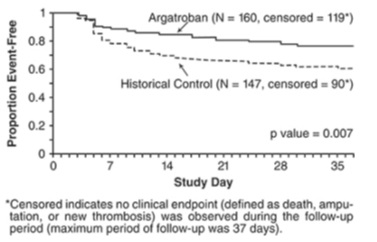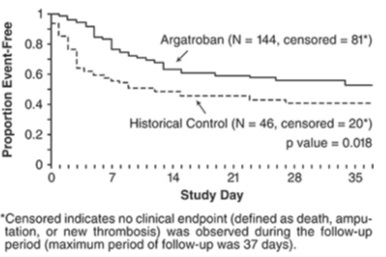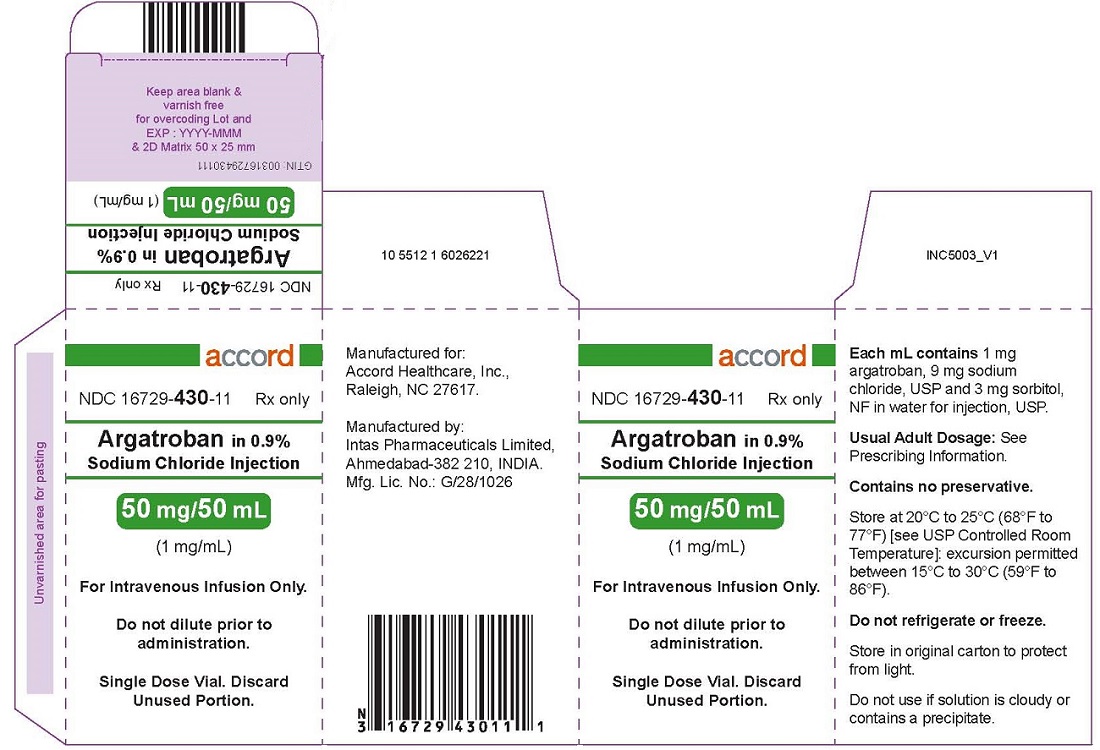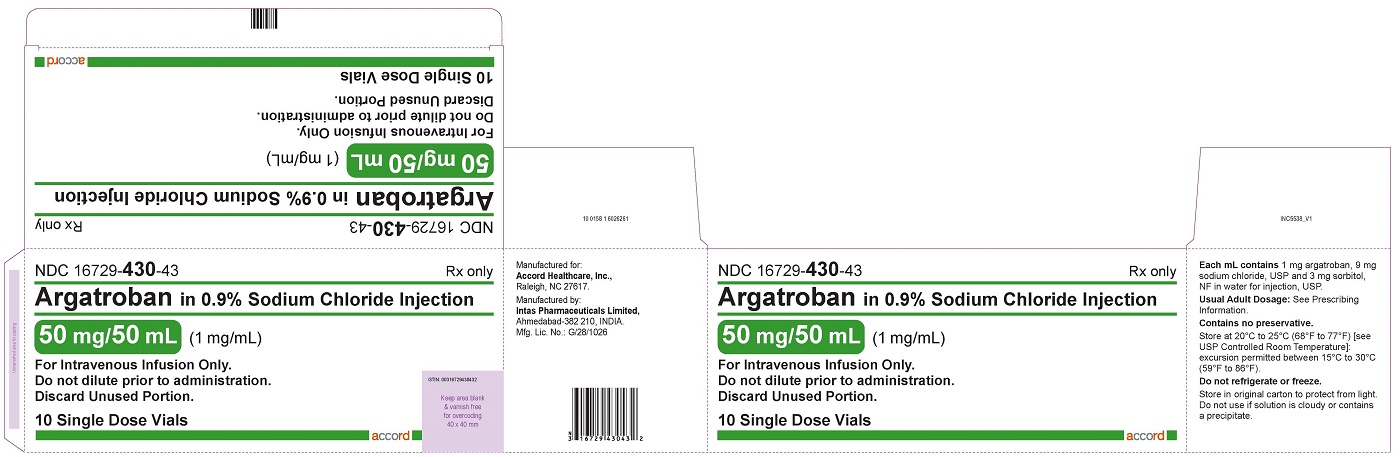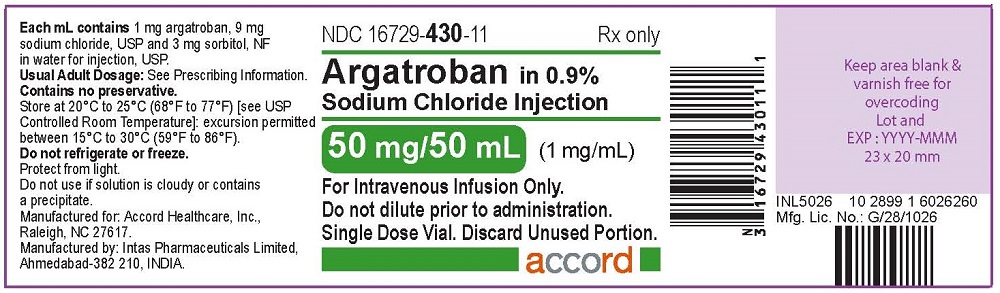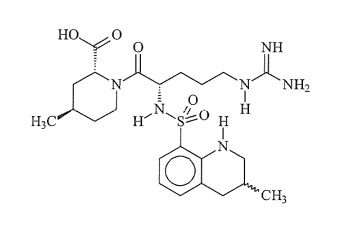 DRUG LABEL: ARGATROBAN
NDC: 16729-430 | Form: INJECTION
Manufacturer: Accord Healthcare Inc.
Category: prescription | Type: HUMAN PRESCRIPTION DRUG LABEL
Date: 20241004

ACTIVE INGREDIENTS: ARGATROBAN 1 mg/1 mL
INACTIVE INGREDIENTS: SODIUM CHLORIDE 9 mg/1 mL; SORBITOL 3 mg/1 mL

HIGHLIGHTS OF PRESCRIBING INFORMATION

These highlights do not include all the information needed to use ARGATROBAN IN SODIUM CHLORIDE INJECTION safely and effectively. See full prescribing information for ARGATROBAN IN SODIUM CHLORIDE INJECTION.
ARGATROBAN IN SODIUM CHLORIDE Injection, for intravenous use
Initial U.S. Approval: 2000

1 INDICATIONS AND USAGE

Argatroban in Sodium Chloride injection is a direct thrombin inhibitor indicated:

- For prophylaxis or treatment of thrombosis in adult patients with heparin-induced thrombocytopenia (HIT) (1.1)
- As an anticoagulant in adult patients with or at risk for HIT undergoing percutaneous coronary intervention (PCI) (1.2)

2 DOSAGE AND ADMINISTRATION

Heparin-Induced Thrombocytopenia(2.2)

The dose for heparin-induced thrombocytopenia without hepatic impairment is 2 mcg/kg/min administered as a continuous infusion

Percutaneous Coronary Intervention(2.3)

The dose for patients with or at risk for heparin-induced thrombocytopenia undergoing percutaneous coronary intervention is started at 25 mcg/kg/min and a bolus of 350 mcg/kg administered via a large bore intravenous line over 3 to 5 minutes

3 DOSAGE FORMS AND STRENGTHS

Injection: 50 mg per 50 mL (1 mg per mL) single-dose vial (3)

4 CONTRAINDICATIONS

- Major bleeding (4)
- History of hypersensitivity to this product (4)

5 WARNINGS AND PRECAUTIONS

- Risk of hemorrhage: Hemorrhage at any site can occur (unexplained fall in hematocrit or blood pressure or other unexplained symptom may indicate hemorrhage). Use with caution in patients at risk, including those receiving antiplatelet agents, thrombolytics, or other anticoagulants (5.1)
- Use in hepatic impairment: Adjust starting dose and titrate carefully in patients with HIT who have moderate or severe hepatic impairment. Avoid use in PCI in patients with clinically significant hepatic impairment (5.2)

6 ADVERSE REACTIONS

- HIT patients: The most common (≥5%) adverse reactions were dyspnea, hypotension, fever, diarrhea, sepsis, and cardiac arrest (6.1)
- PCI patients: The most common (≥5%) adverse reactions were chest pain, hypotension, back pain, nausea, vomiting and headache (6.1)

To report SUSPECTED ADVERSE REACTIONS, contact Accord Healthcare Inc. at 1-866-941-7875 or FDA at 1-800-FDA-1088 or www.fda.gov/medwatch.

7 DRUG INTERACTIONS

- Heparin: Allow sufficient time for heparin's effect on aPTT to decrease before initiating Argatroban in Sodium Chloride Injection therapy (7.1)
- Warfarin: Concomitant use results in increased prolongation of PT and INR (7.2)
- Thrombolytic agents or glycoprotein IIb/IIIa antagonists: Safety and effectiveness of concomitant use with argatroban have not been established (7.4, 7.5)

8 USE IN SPECIFIC POPULATIONS

- Lactation: Discontinue nursing or drug, taking into account the importance of the drug to the mother (8.2)
- Pediatric use: Safety and effectiveness have not been established (8.4)

FULL PRESCRIBING INFORMATION

1 INDICATIONS AND USAGE

1.1 Heparin-Induced Thrombocytopenia

Argatroban in Sodium Chloride Injection is indicated for prophylaxis or treatment of thrombosis in adult patients with heparin-induced thrombocytopenia (HIT).

1.2 Percutaneous Coronary Intervention

Argatroban in Sodium Chloride Injection is indicated as an anticoagulant in adult patients with or at risk for HIT undergoing percutaneous coronary intervention (PCI).

2 DOSAGE AND ADMINISTRATION

2.1 Preparation for Intravenous Administration

Each 50 mL glass vial contains 50 mg of argatroban (1 mg/mL); and, as supplied, is ready for intravenous infusion. Dilution is not required.

Argatroban in Sodium Chloride injection is a clear, colorless to pale yellow solution. Parenteral drug products should be inspected visually for particulate matter and discoloration prior to administration whenever solution and container permit.

Do not use if the solution is cloudy, contains precipitates, or if the flip off seal is not intact.

Vial may be inverted for use with a medical infusion set.

2.2 Dosing in Patients with Heparin-Induced Thrombocytopenia

Initial Dosage

Before administering Argatroban in Sodium Chloride Injection, discontinue heparin therapy and obtain a baseline aPTT. The recommended initial dose of Argatroban in Sodium Chloride Injection for adult patients without hepatic impairment is 2 mcg/kg/min, administered as a continuous infusion
(see Table 1).

Table 1.
Recommended Doses and Infusion Rates for 2 mcg/kg/min Dose
of Argatroban in Sodium Chloride Injection for Patients with HIT* and without
Hepatic Impairment (1 mg/mL Concentration)
Body Weight (kg) | Dose (mcg/min) | Infusion Rate (mL/hr)
50 | 100 | 6
60 | 120 | 7
70 | 140 | 8
80 | 160 | 10
90 | 180 | 11
100 | 200 | 12
110 | 220 | 13
120 | 240 | 14
130 | 260 | 16
140 | 280 | 17
*with or without thrombosis

Monitoring Therapy

For use in HIT, therapy with Argatroban in Sodium Chloride Injection is monitored using the aPTT with a target range of 1.5 to 3 times the initial baseline value (not to exceed 100 seconds). Tests of anticoagulant effects (including the aPTT) typically attain steady-state levels within 1 to 3 hours following initiation of Argatroban in Sodium Chloride Injection. Check the aPTT 2 hours after initiation of therapy and after any dose change to confirm that the patient has attained the desired therapeutic range.

Dosage Adjustment

After the initiation of Argatroban in Sodium Chloride Injection, adjust the dose (not to exceed 10 mcg/kg/min) as necessary to obtain a steady-state aPTT in the target range [see Clinical Studies (14.1)] .

2.3 Dosing in Patients Undergoing Percutaneous Coronary Interventions

Initial Dosage

Initiate an infusion of Argatroban in Sodium Chloride Injection at 25 mcg/kg/min and administer a bolus of 350 mcg/kg via a large bore intravenous line over 3 to 5 minutes (see Table 2). Check an activated clotting time (ACT) 5 to 10 minutes after the bolus dose is completed. The PCI procedure may proceed if the ACT is greater than 300 seconds.

Dosage Adjustment

If the ACT is less than 300 seconds, an additional intravenous bolus dose of 150 mcg/kg should be administered, the infusion dose increased to 30 mcg/kg/min, and the ACT checked 5 to 10 minutes later (see Table 2).

If the ACT is greater than 450 seconds, decrease the infusion rate to 15 mcg/kg/min, and check the ACT 5 to 10 minutes later (Table 3).

Continue titrating the dose until a therapeutic ACT (between 300 and 450 seconds) has been achieved; continue the same infusion rate for the duration of the PCI procedure.

In case of dissection, impending abrupt closure, thrombus formation during the procedure, or inability to achieve or maintain an ACT over 300 seconds, additional bolus doses of 150 mcg/kg may be administered and the infusion dose increased to 40 mcg/kg/min. Check the ACT after each additional bolus or change in the rate of infusion.

Table 2.
Recommended Starting and Maintenance Doses (Within the Target ACT Range) of Argatroban
in Sodium Chloride Injection in Patients Undergoing PCI without Hepatic Impairment
(1 mg/mL Concentration)
Body Weight (kg) | Starting Bolus Dose (350 mcg/kg) |  | Starting and Maintenance Continuous Infusion Dosing For ACT 300-450 seconds 25 mcg/kg/min
Body Weight (kg) | Bolus Dose (mcg) | Bolus Volume (mL) | Continuous Infusion Dose (mcg/min) | Continuous Infusion Rate (mL/hr)
50 | 17,500 | 18 | 1,250 | 75
60 | 21,000 | 21 | 1,500 | 90
70 | 24,500 | 25 | 1,750 | 105
80 | 28,000 | 28 | 2,000 | 120
90 | 31,500 | 32 | 2,250 | 135
100 | 35,000 | 35 | 2,500 | 150
110 | 38,500 | 39 | 2,750 | 165
120 | 42,000 | 42 | 3,000 | 180
130 | 45,500 | 46 | 3,250 | 195
140 | 49,000 | 49 | 3,500 | 210
NOTE: 1 mg = 1000 mcg; 1 kg = 2.2 lbs

Table 3.
Recommended Dose Adjustments of Argatroban in Sodium Chloride Injection for Patients Outside of ACT Target Range Undergoing PCI without Hepatic Impairment (1 mg/mL Concentration)
Body Weight (kg) | If ACT Less than 300 seconds Dosage Adjustment† 30 mcg/kg/min |  |  |  | If ACT Greater than 450 seconds Dosage Adjustment* 15 mcg/kg/min
Body Weight (kg) | Additional Bolus Dose (mcg) | Bolus Volume (mL) | Continuous Infusion Dose (mcg/min) | Continuous Infusion Rate (mL/hr) | Continuous Infusion Dose (mcg/min) | Continuous Infusion Rate (mL/hr)
50 | 7,500 | 8 | 1,500 | 90 | 750 | 45
60 | 9,000 | 9 | 1,800 | 108 | 900 | 54
70 | 10,500 | 11 | 2,100 | 126 | 1,050 | 63
80 | 12,000 | 12 | 2,400 | 144 | 1,200 | 72
90 | 13,500 | 14 | 2,700 | 162 | 1,350 | 81
100 | 15,000 | 15 | 3,000 | 180 | 1,500 | 90
110 | 16,500 | 17 | 3,300 | 198 | 1,650 | 99
120 | 18,000 | 18 | 3,600 | 216 | 1,800 | 108
130 | 19,500 | 20 | 3,900 | 234 | 1,950 | 117
140 | 21,000 | 21 | 4,200 | 252 | 2,100 | 126
NOTE: 1 mg = 1000 mcg; 1 kg = 2.2 lbs
† Additional intravenous bolus dose of 150 mcg/kg should be administered if ACT less than 300 seconds.
* No bolus dose is given if ACT greater than 450 seconds.

Monitoring Therapy

For use in PCI, therapy with Argatroban in Sodium Chloride Injection is monitored using ACT. Obtain ACTs before dosing, 5 to 10 minutes after bolus dosing, following adjustments in the infusion rate, and at the end of the PCI procedure. Obtain additional ACTs every 20 to 30 minutes during a prolonged procedure.

Continued Anticoagulation after PCI

If a patient requires anticoagulation after the procedure, Argatroban in Sodium Chloride Injection may be continued, but at a rate of 2 mcg/kg/min and adjusted as needed to maintain the aPTT in the desired range [see Dosage and Administration (2.2)] .

2.4 Dosing in Patients with Hepatic Impairment

For adult patients with HIT and moderate or severe hepatic impairment (based on Child-Pugh classification), an initial dose of 0.5 mcg/kg/min is recommended, based on the approximately 4-fold decrease in argatroban clearance relative to those with normal hepatic function. Monitor the aPTT closely, and adjust the dosage as clinically indicated.

Monitoring Therapy

Achievement of steady state aPTT levels may take longer and require more dose adjustments in patients with hepatic impairment compared to patients with normal hepatic function.

For patients with hepatic impairment undergoing PCI and who have HIT or are at risk for HIT, carefully titrate argatroban until the desired level of anticoagulation is achieved. Use of Argatroban in PCI patients with clinically significant hepatic disease or AST/ALT levels ≥3 times the upper limit of normal should be avoided [see Warnings and Precautions (5.2)] .

2.5 Conversion to Oral Anticoagulant Therapy

Initiating Oral Anticoagulant Therapy

When converting patients from Argatroban in Sodium Chloride Injection to oral anticoagulant therapy, consider the potential for combined effects on International Normalized Ratio (INR). To avoid prothrombotic effects and to ensure continuous anticoagulation when initiating warfarin, overlap Argatroban in Sodium Chloride Injection and warfarin therapy. There are insufficient data available to recommend the duration of the overlap. Initiate therapy using the expected daily dose of warfarin. A loading dose of warfarin should not be used.

The relationship between INR and bleeding risk is altered when argatroban and warfarin are co-administered. The combination of argatroban and warfarin does not cause further reduction in the vitamin-K dependent factor Xa activity than that which is seen with warfarin alone. The relationship between INR obtained on combined therapy and INR obtained on warfarin alone is dependent on both the dose of argatroban and the thromboplastin reagent used. The INR value on warfarin alone (INRw) can be calculated from the INR value on combination argatroban and warfarin therapy [see Drug Interactions (7.2)and Clinical Pharmacology (12.2)] .

Co-Administration of Warfarin and Argatroban in Sodium Chloride injection at Doses Up to 2 mcg/kg/min:

Measure INR daily while Argatroban in Sodium Chloride Injection and warfarin are co-administered. In general, with doses of Argatroban in Sodium Chloride Injection up to 2 mcg/kg/min, Argatroban in Sodium Chloride Injection can be discontinued when the INR is > 4 on combined therapy. After Argatroban in Sodium Chloride Injection is discontinued, repeat the INR measurement in 4 to 6 hours. If the repeat INR is below the desired therapeutic range, resume the infusion of Argatroban in Sodium Chloride Injection and repeat the procedure daily until the desired therapeutic range on warfarin alone is reached.

Co-Administration of Warfarin and Argatroban in Sodium Chloride injection at Doses Greater than 2 mcg/kg/min:

For doses greater than 2 mcg/kg/min, the relationship of INR between warfarin alone to the INR on warfarin plus argatroban is less predictable. In this case, in order to predict the INR on warfarin alone, temporarily reduce the dose of Argatroban in Sodium Chloride Injection to a dose of 2 mcg/kg/min. Repeat the INR on Argatroban in Sodium Chloride Injection and warfarin 4 to 6 hours after reduction of the Argatroban in Sodium Chloride Injection dose and follow the process outlined above for administering Argatroban in Sodium Chloride Injection at doses up to 2 mcg/kg/min.

3 DOSAGE FORMS AND STRENGTHS

Injection: 50 mg per 50 mL (1mg per mL) a single–dose vial. The solution is ready for intravenous infusion.

4 CONTRAINDICATIONS

Argatroban is contraindicated in:

- Patients with major bleeding [see Warnings and Precautions (5.1)].
- Patients with a history of hypersensitivity to argatroban. Airway, skin, and generalized hypersensitivity reactions have been reported [see Adverse Reactions (6.1)] .

5 WARNINGS AND PRECAUTIONS

5.1 Risk of Hemorrhage

Hemorrhage can occur at any site in the body in patients receiving argatroban [ see Adverse Reactions (6.1)]. An unexplained fall in hematocrit or hemoglobin or a fall in blood pressure should lead to consideration of a hemorrhagic event. Argatroban in Sodium Chloride Injection should be used with extreme caution in disease states and other circumstances in which there is an increased danger of hemorrhage. These include severe hypertension; immediately following lumbar puncture; spinal anesthesia; major surgery, especially involving the brain, spinal cord, or eye; hematologic conditions associated with increased bleeding tendencies such as congenital or acquired bleeding disorders and gastrointestinal lesions such as ulcerations.

Concomitant use of argatroban with antiplatelet agents, thrombolytics, and other anticoagulants may increase the risk of bleeding.

5.2 Use in Hepatic Impairment

When administering Argatroban in Sodium Chloride Injection to patients with hepatic impairment, start with a lower dose and carefully titrate until the desired level of anticoagulation is achieved. Achievement of steady-state aPTT levels may take longer and require more argatroban dose adjustments in patients with hepatic impairment compared to patients with normal hepatic function [see Use in Specific Populations (8.6)]. Also, upon cessation of argatroban infusion in the hepatically impaired patient, full reversal of anticoagulant effects may require longer than 4 hours due to decreased clearance and increased elimination half-life of argatroban [see Dosage and Administration (2.4)and Clinical Pharmacology (12.3)]. Avoid the use of high doses of Argatroban in Sodium Chloride Injection in patients undergoing PCI who have clinically significant hepatic disease or AST/ALT levels ≥3 times the upper limit of normal.

5.3 Laboratory Tests

Anticoagulation effects associated with argatroban infusion at doses up to 40 mcg/kg/min correlate with increases of the activated partial thromboplastin time (aPTT). Although other global clot-based tests including prothrombin time (PT), the International Normalized Ratio (INR), and thrombin time (TT) are affected by argatroban, the therapeutic ranges for these tests have not been identified for argatroban therapy. In clinical trials in PCI, the activated clotting time (ACT) was used for monitoring argatroban anticoagulant activity during the procedure. The concomitant use of argatroban and warfarin results in prolongation of the PT and INR beyond that produced by warfarin alone [see Dosage and Administration (2.5)and Clinical Pharmacology (12.2)] .

6 ADVERSE REACTIONS

The following clinically significant adverse reactions are described elsewhere in the labeling:

- Risk of Hemorrhage [see Warnings and Precautions (5.1)]

6.1 Clinical Trials Experience

Because clinical trials are conducted under widely varying conditions, adverse event rates observed in the clinical trials of a drug cannot be directly compared to rates in the clinical trials of another drug and may not reflect the rates observed in practice.

Adverse Reactions in Patients with HIT (With or Without Thrombosis)

The following safety information is based on all 568 patients treated with argatroban in Study 1 and Study 2. The safety profile of the patients from these studies is compared with that of 193 historical controls in which the adverse reactions were collected retrospectively. Adverse reactions are separated into hemorrhagic and non-hemorrhagic reactions.

Major bleeding was defined as bleeding that was overt and associated with a hemoglobin decrease ≥2 g/dL, that led to a transfusion of ≥2 units, or that was intracranial, retroperitoneal, or into a major prosthetic joint. Minor bleeding was overt bleeding that did not meet the criteria for major bleeding.

Table 4gives an overview of the most frequently observed hemorrhagic reactions, presented separately by major and minor bleeding, sorted by decreasing occurrence among argatroban-treated patients with HIT (with or without thrombosis).

Table 4.
Major and Minor Hemorrhagic Adverse Reactions in Patients With HIT*
 | Argatroban-treated Patients (Study 1 and Study 2) (n = 568) % | Historical Controlc (n = 193) %
Major Hemorrhagic Reactionsa
Overall bleeding | 5.3 | 6.7
Gastrointestinal | 2.3 | 1.6
Genitourinary and hematuria | 0.9 | 0.5
Decrease in hemoglobin and hematocrit | 0.7 | 0
Multisystem hemorrhage and DIC | 0.5 | 1
Limb and BKA stump | 0.5 | 0
Intracranial hemorrhage | 0b | 0.5
Minor Hemorrhagic Reactionsa
Gastrointestinal | 14.4 | 18.1
Genitourinary and hematuria | 11.6 | 0.8
Decrease in hemoglobin and hematocrit | 10.4 | 0
Groin | 5.4 | 3.1
Hemoptysis | 2.9 | 0.8
Brachial | 2.4 | 0.8
*with or without thrombosis
a) Patients may have experienced more than 1 adverse reaction.
b) One patient experienced intracranial hemorrhage 4 days after discontinuation of argatroban and following therapy with urokinase and oral anticoagulation.
c) The historical control group consisted of patients with a clinical diagnosis of HIT (with or without thrombosis) that were considered eligible by an independent medical panel.
DIC = disseminated intravascular coagulation.
BKA = below-the-knee amputation

Table 5gives an overview of the most frequently observed non-hemorrhagic reactions sorted by decreasing frequency of occurrence (≥2%) among argatroban-treated HIT/HITTS patients.

Table 5.
Non-hemorrhagic Adverse Reactions in PatientsaWith HITb
 | Argatroban-treated Patients (Study 1 and Study 2) (n = 568) % | Historical Controlc (n = 193) %
Dyspnea | 8.1 | 8.8
Hypotension | 7.2 | 2.6
Fever | 6.9 | 2.1
Diarrhea | 6.2 | 1.6
Sepsis | 6 | 12.4
Cardiac arrest | 5.8 | 3.1
Nausea | 4.8 | 0.5
Ventricular tachycardia | 4.8 | 3.1
Pain | 4.6 | 3.1
Urinary tract infection | 4.6 | 5.2
Vomiting | 4.2 | 0
Infection | 3.7 | 3.6
Pneumonia | 3.3 | 9.3
Atrial fibrillation | 3 | 11.4
Coughing | 2.8 | 1.6
Abnormal renal function | 2.8 | 4.7
Abdominal pain | 2.6 | 1.6
Cerebrovascular disorder | 2.3 | 4.1
a) Patients may have experienced more than 1 adverse reaction.
b) with or without thrombosis
c) The historical control group consisted of patients with a clinical diagnosis of HIT (with or without thrombosis) that were considered eligible by an independent medical panel.

Adverse Reactions in Patients with or at Risk for HIT Patients Undergoing PCI

The following safety information is based on 91 patients initially treated with argatroban and 21 patients subsequently re-exposed to argatroban for a total of 112 PCIs with argatroban anticoagulation. Adverse reactions are separated into hemorrhagic (Table 6) and non-hemorrhagic (Table 7) reactions.

Major bleeding was defined as bleeding that was overt and associated with a hemoglobin decrease ≥5 g/dL, that led to transfusion of ≥2 units, or that was intracranial, retroperitoneal, or into a major prosthetic joint.

The rate of major bleeding reactions in patients treated with argatroban in the PCI trials was 1.8%.

Table 6.
Major and Minor Hemorrhagic Adverse Reactions in Patients With HIT Undergoing PCI
Major Hemorrhagic Reactionsa
 | Argatroban-treated Patients (n = 112)b %
Retroperitoneal | 0.9
Gastrointestinal | 0.9
Intracranial | 0
Minor Hemorrhagic Reactionsa
Groin (bleeding or hematoma) | 3.6
Gastrointestinal (includes hematemesis) | 2.6
Genitourinary (includes hematuria) | 1.8
Decrease in hemoglobin and/or hematocrit | 1.8
CABG (coronary arteries) | 1.8
Access site | 0.9
Hemoptysis | 0.9
Other | 0.9
a) Patients may have experienced more than 1 adverse reaction.
b) 91 patients who underwent 112 interventions.
CABG = coronary artery bypass graft

Table 7gives an overview of the most frequently observed non-hemorrhagic reactions (>2%), sorted by decreasing frequency of occurrence among argatroban-treated PCI patients.

Table 7.
Non-hemorrhagic Adverse Reactionsain Patients With HIT Undergoing PCI
 | Argatroban Proceduresa (n = 112) b %
Chest pain | 15.2
Hypotension | 10.7
Back pain | 8
Nausea | 7.1
Vomiting | 6.3
Headache | 5.4
Bradycardia | 4.5
Abdominal pain | 3.6
Fever | 3.6
Myocardial infarction | 3.6
a) Patients may have experienced more than 1 adverse reaction.
b) 91 patients who underwent 112 interventions.

There were 22 serious adverse reactions in 17 PCI patients (19.6% in 112 interventions). Table 8lists the serious adverse reactions occurring in argatroban-treated-patients with or at risk for HIT undergoing PCI.

Table 8.
Serious Adverse Reaction in Patients With HIT Undergoing PCIa
Adverse Reaction | Argatroban Proceduresb (n = 112)
Myocardial infarction | 4 (3.5%)
Angina pectoris | 2 (1.8%)
Coronary thrombosis | 2 (1.8%)
Myocardial ischemia | 2 (1.8%)
Occlusion coronary | 2 (1.8%)
Chest pain | 1 (0.9%)
Fever | 1 (0.9%)
Retroperitoneal hemorrhage | 1 (0.9%)
Aortic stenosis | 1 (0.9%)
Arterial thrombosis | 1 (0.9%)
Gastrointestinal hemorrhage | 1 (0.9%)
Gastrointestinal disorder (GERD) | 1 (0.9%)
Cerebrovascular disorder | 1 (0.9%)
Lung edema disorder | 1 (0.9%)
Vascular disorder | 1 (0.9%)
a) Individual reactions may also have been reported elsewhere (see Table 6and Table 7).
b) 91 patients underwent 112 procedures. Some patients may have experienced more than 1 reaction.

Intracranial Bleeding in Other Populations

Increased risks for intracranial bleeding have been observed in investigational studies of argatroban for other uses. In a study of patients with acute myocardial infarction receiving both argatroban and thrombolytic therapy (streptokinase or tissue plasminogen activator), the overall frequency of intracranial bleeding was 1% (8 out of 810 patients). Intracranial bleeding was not observed in 317 subjects or patients who did not receive concomitant thrombolysis [see Drug Interactions (7.4)] .

The safety and effectiveness of argatroban for cardiac indications other than PCI in patients with HIT have not been established. Intracranial bleeding was also observed in a prospective, placebo-controlled study of argatroban in patients who had onset of acute stroke within 12 hours of study entry. Symptomatic intracranial hemorrhage was reported in 5 of 117 patients (4.3%) who received argatroban at 1 to 3 mcg/kg/min and in none of the 54 patients who received placebo. Asymptomatic intracranial hemorrhage occurred in 5 (4.3%) and 2 (3.7%) of the patients, respectively.

Allergic Reactions

One hundred fifty-six allergic reactions or suspected allergic reactions were observed in 1,127 individuals who were treated with argatroban in clinical pharmacology studies or for various clinical indications. About 95% (148/156) of these reactions occurred in patients who concomitantly received thrombolytic therapy (e.g., streptokinase) or contrast media.

Allergic reactions or suspected allergic reactions in populations other than patients with HIT (with or without thrombosis) include (in descending order of frequency):

- Airway reactions (coughing, dyspnea): 10% or more
- Skin reactions (rash, bullous eruption): 1 to <10%
- General reactions (vasodilation): 1 to 10%

Limited data are available on the potential formation of drug-related antibodies. Plasma from 12 healthy volunteers treated with argatroban over 6 days showed no evidence of neutralizing antibodies. No loss of anticoagulant activity was noted with repeated administration of argatroban to more than 40 patients.

7 DRUG INTERACTIONS

7.1 Heparin

If argatroban is to be initiated after cessation of heparin therapy, allow sufficient time for heparin's effect on the aPTT to decrease prior to initiation of argatroban therapy.

7.2 Oral Anticoagulant Agents

Pharmacokinetic drug-drug interactions between argatroban and warfarin (7.5 mg single oral dose) have not been demonstrated. However, the concomitant use of argatroban and warfarin (5 to 7.5 mg initial oral dose, followed by 2.5 to 6 mg/day orally for 6 to 10 days) results in prolongation of the prothrombin time (PT) and International Normalized Ratio (INR) [see Dosage and Administration (2.5)and Clinical Pharmacology (12.2)] .

7.3 Aspirin/Acetaminophen

No drug-drug interactions have been demonstrated between argatroban and concomitantly administered aspirin or acetaminophen [see Clinical Pharmacology (12.3)] .

7.4 Thrombolytic Agents

The safety and effectiveness of argatroban with thrombolytic agents have not been established [see Adverse Reactions (6.1)] .

7.5 Glycoprotein IIb/IIIa Antagonists

The safety and effectiveness of argatroban with glycoprotein IIb/IIIa antagonists have not been established.

8 USE IN SPECIFIC POPULATIONS

8.1 Pregnancy

Risk Summary

Limited data from published literature and postmarketing reports do not suggest an association between argatroban and adverse fetal outcomes. There are risks to the mother associated with untreated thrombosis in pregnancy and a risk of hemorrhage in the mother and fetus associated with the use of anticoagulants (see Clinical Considerations) . In animal reproduction studies, there was no evidence of adverse developmental outcomes with intravenous administration of argatroban in rats and rabbits at doses up to 0.3-and 0.2-times, respectively, the maximum recommended human dose (MHRD) (see Data).

The estimated background risk of major birth defects and miscarriage for the indicated population is unknown. All pregnancies have a background risk of birth defect, loss, or other adverse outcomes. In the U.S. general population, the estimated background risk of major birth defects and miscarriage in clinically recognized pregnancies is 2% to 4% and 15% to 20% respectively.

Clinical Considerations

Disease-Associated Maternal and/or Embryo/Fetal Risk

Pregnancy confers an increased risk for thromboembolism that is higher for women with underlying thromboembolic disease and certain high-risk pregnancy conditions. Published data describe that women with a previous history of venous thrombosis are at high risk for recurrence during pregnancy.

Fetal/Neonatal Adverse Reactions

Use of anticoagulants, including argatroban, may increase the risk of bleeding in the fetus and neonate. Monitor neonates for bleeding [see Warnings and Precautions (5.1, 5.3)].

Labor or Delivery

All patients receiving anticoagulants, including pregnant women, are at risk for bleeding. Pregnant women receiving argatroban should be carefully monitored for evidence of excessive bleeding or unexpected changes in coagulation parameters [see Warnings and Precautions (5.1, 5.3)].

Data

Animal data

Developmental studies performed in rats (during gestation Days 7 to 17) with argatroban at intravenous doses up to 27 mg/kg/day (0.3 times the maximum recommended human dose, based on body surface area) and in rabbits (during gestation Days 6 to 18) at intravenous doses up to 10.8 mg/kg/day (0.2 times the maximum recommended human dose, based on body surface area) have revealed no evidence of harm to the fetus.

8.2 Lactation

Risk Summary

There are no data on the presence of argatroban in human milk, or its effects on milk production. Argatroban is present in rat milk. The developmental and health benefits of breastfeeding should be considered along with the mother’s clinical need for Argatroban in Sodium Chloride Injection and any potential adverse effects on the breastfed infant from Argatroban or from the underlying maternal condition.

Data

Argatroban is detected in rat milk.

8.4 Pediatric Use

Safety and effectiveness have not been established in pediatric patients.

Argatroban was studied among 18 seriously ill pediatric patients who required an alternative to heparin anticoagulation. Most patients were diagnosed with HIT or suspected HIT. Age ranges of patients were <6 months, n = 8; six months to <8 years, n = 6; 8 to 16 years, n = 4. All patients had serious underlying conditions and were receiving multiple concomitant medications. Thirteen patients received argatroban solely as a continuous infusion (no bolus dose). Dosing was initiated in the majority of these 13 patients at 1 mcg/kg/min and subsequently titrated as needed to achieve and maintain an aPTT of 1.5 to 3 times the baseline value. Most patients required multiple dose adjustments to maintain anticoagulation parameters within the desired range. During the 30-day study period, thrombotic events occurred during argatroban administration to two patients: one patient experienced an intracranial hemorrhage after 4 days of argatroban therapy in the setting of sepsis and thrombocytopenia and another patient experienced an intracranial hemorrhage after receiving argatroban for greater than 14 days. The study findings did not establish the safe and effective use of argatroban in pediatric patients and the dosing of 1 mcg/kg/min was not supported by the pharmacometric data described below.

Pediatric Pharmacokinetics (PK) and Pharmacodynamics (PD)

PK parameters of argatroban were characterized in population PK/PD analysis model with sparse data from 15 seriously ill pediatric patients. Argatroban clearance in these seriously ill pediatric patients (0.16 L/hr/kg) was 50% lower compared to argatroban clearance in healthy adults (0.31 L/hr/kg). Four pediatric patients with elevated bilirubin (secondary to cardiac complications or hepatic impairment) had, on average, 80% lower clearance (0.03 L/hr/kg) when compared to pediatric patients with normal bilirubin levels.

These PK/PD analysis models based on a goal of aPTT prolongation of 1.5 to 3 times the baseline value and avoidance of an aPTT > 100 seconds for seriously ill pediatric patients with HIT/HITTS who require an alternative to heparin suggested the following:

- For patients with normal hepatic function,a starting infusion rate of 0.75 mcg/kg/min may have comparable aPTT responses as a starting dose of 2 mcg/kg/min in health adults. Additionally, based on an evaluation of aPTT every two hours, increasing the dosage by 0.1 to 0.25 mcg/kg/min could achieve additional aPTT responses.
- For patients with hepatic impairmenta starting infusion rate of 0.2 mcg/kg/min with increasing dosing by increments of 0.05 mcg/kg/min may have comparable argatroban exposure as expected with adult doses.

The safety and effectiveness of argatroban with the above dosing have not been adequately assessed in pediatric patients and the safety and effectiveness of argatroban is not established in pediatric patients. In addition, the described dosage did not take into account multiple factors that could affect the dosage such as current aPTT, target aPTT, and the clinical status of the patient.

8.5 Geriatric Use

Of the total number of subjects (1340) in clinical studies of argatroban, 35% were 65 and over. In the clinical studies of adult patients with HIT (with or without thrombosis), the effectiveness of argatroban was not affected by age. No trends were observed across age groups for both aPTT and the ACT. The safety analysis did suggest that older patients tended to have an increased incidence of adverse reactions compared to younger patients; however, older patients had increased underlying conditions, which may predispose them to adverse reactions. The studies were not sized appropriately to detect differences in safety between age groups.

8.6 Hepatic Impairment

Dose reduction and careful titration are required when administering argatroban to patients with hepatic impairment. Reversal of anticoagulation effect may be prolonged in this population [see Dosage and Administration (2.4), Warnings and Precautions (5.2), Clinical Pharmacology (12.3)] .

10 OVERDOSAGE

Excessive anticoagulation, with or without bleeding, may be controlled by discontinuing argatroban or by decreasing the argatroban dose. In clinical studies, anticoagulation parameters generally returned from therapeutic levels to baseline within 2 to 4 hours after discontinuation of the drug. Reversal of anticoagulant effect may take longer in patients with hepatic impairment.

No specific antidote to argatroban is available; if life- threatening bleeding occurs and excessive plasma levels of argatroban are suspected, discontinue argatroban immediately and measure aPTT and other coagulation parameters. When argatroban was administered as a continuous infusion (2 mcg/kg/min) prior to and during a 4-hour hemodialysis session, approximately 20% of argatroban was cleared through dialysis.

Single intravenous doses of argatroban at 200, 124, 150, and 200 mg/kg were lethal to mice, rats, rabbits, and dogs, respectively. The symptoms of acute toxicity were loss of righting reflex, tremors, clonic convulsions, paralysis of hind limbs, and coma.

11 DESCRIPTION

Argatroban is a synthetic direct thrombin inhibitor. The chemical name is 1-[(2S)-5-[(aminoimino-methyl)amino]-1-oxo-2-[[(1,2,3,4-tetrahydro-3-methyl-8-quinolinyl)sulfonyl]amino]pentyl]-4-methyl-,(2R,4R)- 2-Piperidinecarboxylic acid. Argatroban has 4 asymmetric carbons. One of the asymmetric carbons has an Rconfiguration (stereoisomer Type I) and an Sconfiguration (stereoisomer Type II). Argatroban consists of a mixture of Rand Sstereoisomers at a ratio of approximately 65:35.

The molecular formula of argatroban is C23H36N6O5S. Its molecular weight is 508.63 g/mol. The structural formula is:

Argatroban in Sodium Chloride Injection is a sterile, non-pyrogenic, clear, colorless to pale yellow isotonic solution. It is supplied in a single-dose clear glass vial containing 50 mg of argatroban in 50 mL sodium chloride solution. Each mL contains 1 mg argatroban, 9 mg sodium chloride, USP and 3 mg sorbitol, NF in water for injection, USP. The pH of the solution is between 3.2 to 7.5.

12 CLINICAL PHARMACOLOGY

12.1 Mechanism of Action

Argatroban is a direct thrombin inhibitor that reversibly binds to the thrombin active site. Argatroban does not require the co-factor antithrombin III for antithrombotic activity. Argatroban exerts its anticoagulant effects by inhibiting thrombin-catalyzed or –induced reactions, including fibrin formation; activation of coagulation factors V, VIII, and XIII; activation of protein C; and platelet aggregation.

Argatroban inhibits thrombin with an inhibition constant (Ki) of 0.04 μM. At therapeutic concentrations, argatroban has little or no effect on related serine proteases (trypsin, factor Xa, plasmin, and kallikrein).

Argatroban is capable of inhibiting the action of both free and clot-associated thrombin.

12.2 Pharmacodynamics

When argatroban is administered by continuous infusion, anticoagulant effects and plasma concentrations of argatroban follow similar, predictable temporal response profiles, with low intersubject variability. Immediately upon initiation of argatroban infusion, anticoagulant effects are produced as plasma argatroban concentrations begin to rise. Steady-state levels of both drug and anticoagulant effect are typically attained within 1 to 3 hours and are maintained until the infusion is discontinued or the dosage adjusted. Steady-state plasma argatroban concentrations increase proportionally with dose (for infusion doses up to 40 mcg/kg/min in healthy subjects) and are well correlated with steady-state anticoagulant effects. For infusion doses up to 40 mcg/kg/min, argatroban increases in a dose-dependent fashion, the activated partial thromboplastin time (aPTT), the activated clotting time (ACT), the prothrombin time (PT), the International Normalized Ratio (INR), and the thrombin time (TT) in healthy volunteers and cardiac patients. Representative steady-state plasma argatroban concentrations and anticoagulant effects are shown below for argatroban infusion doses up to 10 mcg/kg/min (see Figure 1).

Figure 1.
Relationship at Steady State Between Argatroban Dose, Plasma Argatroban
Concentration and Anticoagulant Effect

Effect on International Normalized Ratio (INR):Because argatroban is a direct thrombin inhibitor, co-administration of argatroban and warfarin produces a combined effect on the laboratory measurement of the INR. However, concurrent therapy, compared to warfarin monotherapy, exerts no additional effect on vitamin K-dependent factor Xa activity.

The relationship between INR on co-therapy and warfarin alone is dependent on both the dose of argatroban and the thromboplastin reagent used. This relationship is influenced by the International Sensitivity Index (ISI) of the thromboplastin. Data for 2 commonly utilized thromboplastins with ISI values of 0.88 (Innovin, Dade) and 1.78 (Thromboplastin C Plus, Dade) are presented in Figure 2for an argatroban dose of 2 mcg/kg/min. Thromboplastins with higher ISI values than shown result in higher INRs on combined therapy of warfarin and argatroban. These data are based on results obtained in normal individuals [see Dosage and Administration (2.5), Warnings and Precautions (5.3)] .

Figure 2.
INR Relationship of Argatroban Plus Warfarin Versus Warfarin Alone

Figure 2demonstrates the relationship between INR for warfarin alone and INR for warfarin co-administered with argatroban at a dose of 2 mcg/kg/min. To calculate INR for warfarin alone (INRW), based on INR for co-therapy of warfarin and argatroban (INRWA), when the argatroban dose is 2 mcg/kg/min, use the equation next to the appropriate curve. Example: At a dose of 2 mcg/kg/min and an INR performed with Thromboplastin A, the equation 0.19 + 0.57 (INRWA) = INRWwould allow a prediction of the INR on warfarin alone (INRW). Thus, using an INRWAvalue of 4 obtained on combined therapy: INRW= 0.19 + 0.57 (4) = 2.47 as the value for INR on warfarin alone. The error (confidence interval) associated with a prediction is ± 0.4 units. Similar linear relationships and prediction errors exist for argatroban at a dose of 1 mcg/kg/min. Thus, for argatroban doses of 1 or 2 mcg/kg/min, INRWcan be predicted from INRWA. For argatroban doses greater than 2 mcg/kg/min, the error associated with predicting INRWfrom INRWAis ± 1. Thus, INRWcannot be reliably predicted from INRWAat doses greater than 2 mcg/kg/min.

12.3 Pharmacokinetics

Distribution

Argatroban distributes mainly in the extra cellular fluid as evidenced by an apparent steady-state volume of distribution of 174 mL/kg (12.18 L in a 70 kg adult). Argatroban is 54% bound to human serum proteins, with binding to albumin and α1– acid glycoprotein being 20% and 34%, respectively.

Metabolism

The main route of argatroban metabolism is hydroxylation and aromatization of the 3-methyltetrahydroquinoline ring in the liver. The formation of each of the 4 known metabolites is catalyzed in vitroby the human liver microsomal cytochrome P450 enzymes CYP3A4/5. The primary metabolite (M1) exerts 3- to 5-fold weaker anticoagulant effects than argatroban. Unchanged argatroban is the major component in plasma. The plasma concentrations of M1 range between 0% and 20% of that of the parent drug. The other metabolites (M2 to M4) are found only in very low quantities in the urine and have not been detected in plasma or feces. These data, together with the lack of effect of erythromycin (a potent CYP3A4/5 inhibitor) on argatroban pharmacokinetics, suggest that CYP3A4/5-mediated metabolism is not an important elimination pathway in vivo.

Total body clearance is approximately 5.1 mL/kg/min (0.31 L/kg/hr) for infusion doses up to 40 mcg/kg/min. The terminal elimination half-life of argatroban ranges between 39 and 51 minutes.

There is no interconversion of the 21-(R):21-(S) diastereoisomers. The plasma ratio of these diastereoisomers is unchanged by metabolism or hepatic impairment, remaining constant at 65:35 (± 2%).

Excretion

Argatroban is excreted primarily in the feces, presumably through biliary secretion. In a study in which^14C-argatroban (5 mcg/kg/min) was infused for 4 hours into healthy subjects, approximately 65% of the radioactivity was recovered in the feces within 6 days of the start of infusion with little or no radioactivity subsequently detected. Approximately 22% of the radioactivity appeared in the urine within 12 hours of the start of infusion. Little or no additional urinary radioactivity was subsequently detected. Average percent recovery of unchanged drug, relative to total dose, was 16% in urine and at least 14% in feces.

Special Populations

Hepatic Impairment: The dosage of argatroban should be decreased in patients with hepatic impairment [ see Dosage and Administration (2.4)and Warnings and Precautions (5.2)]. Patients with hepatic impairment were not studied in percutaneous coronary intervention (PCI) trials. At a dose of 2.5 mcg/kg/min, hepatic impairment is associated with decreased clearance and increased elimination half-life of argatroban (to 1.9 mL/kg/min and 181 minutes, respectively, for patients with a Child-Pugh score >6).

Renal Impairment: No dosage adjustment is necessary in patients with renal dysfunction. The effect of renal disease on the pharmacokinetics of argatroban was studied in 6 subjects with normal renal function (mean Clcr = 95±16 mL/min) and in 18 subjects with mild (mean Clcr = 64±10 mL/min), moderate (mean Clcr = 41±5.8 mL/min), and severe (mean Clcr = 5±7 mL/min) renal impairment. The pharmacokinetics and pharmacodynamics of argatroban at dosages up to 5 mcg/kg/min were not significantly affected by renal dysfunction.

Use of argatroban was evaluated in a study of 12 patients with stable end-stage renal disease undergoing chronic intermittent hemodialysis. Argatroban was administered at a rate of 2 to 3 mcg/kg/min (begun at least 4 hours prior to dialysis) or as a bolus dose of 250 mcg/kg at the start of dialysis followed by a continuous infusion of 2 mcg/kg/min. Although these regimens did not achieve the goal of maintaining ACT values at 1.8 times the baseline value throughout most of the hemodialysis period, the hemodialysis sessions were successfully completed with both of these regimens. The mean ACTs produced in this study ranged from 1.39 to 1.82 times baseline, and the mean aPTTs ranged from 1.96 to 3.4 times baseline. When argatroban was administered as a continuous infusion of 2 mcg/kg/min prior to and during a 4-hour hemodialysis session, approximately 20% was cleared through dialysis.

Age, Gender: There are no clinically significant effects of age or gender on the pharmacokinetics or pharmacodynamics (e.g., aPTT) of argatroban in adults.

Drug-Drug Interactions

Digoxin: In 12 healthy volunteers, intravenous infusion of argatroban (2 mcg/kg/min) over 5 days (study days 11 to 15) did not affect the steady-state pharmacokinetics of oral digoxin (0.375 mg daily for 15 days).

Erythromycin: In 10 healthy subjects, orally administered erythromycin (a potent inhibitor of CYP3A4/5) at 500 mg four times daily for 7 days had no effect on the pharmacokinetics of argatroban at a dose of 1 mcg/kg/min for 5 hours. These data suggest oxidative metabolism by CYP3A4/5 is not an important elimination pathway in vivofor argatroban.

Aspirin and Acetaminophen: Drug-drug interactions have not been demonstrated between argatroban and concomitantly administered aspirin (162.5 mg orally given 26 and 2 hours prior to initiation of argatroban 1 mcg/kg/min over 4 hours) or acetaminophen (1,000 mg orally given 12, 6, and 0 hours prior to, and 6 and 12 hours subsequent to, initiation of argatroban 1.5 mcg/kg/min over 18 hours).

13 NONCLINICAL TOXICOLOGY

13.1 Carcinogenesis, Mutagenesis, Impairment of Fertility

Carcinogenicity studies with argatroban have not been performed.

Argatroban was not genotoxic in the Ames test, the Chinese hamster ovary cell (CHO/HGPRT) forward mutation test, the Chinese hamster lung fibroblast chromosome aberration test, the rat hepatocyte, and WI-38 human fetal lung cell unscheduled DNA synthesis (UDS) tests, or the mouse micronucleus test.

Argatroban at intravenous doses up to 27 mg/kg/day (0.3 times the recommended maximum human dose based on body surface area) had no effect on fertility and reproductive function of male and female rats.

14 CLINICAL STUDIES

14.1 Heparin-Induced Thrombocytopenia

The safety and efficacy of argatroban were evaluated in an historically controlled efficacy and safety study (Study 1) and a follow-on efficacy and safety study (Study 2). These studies were comparable with regard to study design, study objectives, dosing regimens as well as study outline, conduct, and monitoring. In these studies, 568 adult patients were treated with argatroban and 193 adult patients made up the historical control group. Patients had a clinical diagnosis of heparin-induced thrombocytopenia, either without thrombosis (HIT) or with thrombosis (HITTS [heparin-induced thrombocytopenia and thrombosis syndrome]) and were males or non-pregnant females between the ages of 18 and 80 years old. HIT/HITTS was defined by a fall in platelet count to less than 100,000/μL or a 50% decrease in platelets after the initiation of heparin therapy with no apparent explanation other than HIT. Patients with HITTS also had an arterial or venous thrombosis documented by appropriate imaging techniques or supported by clinical evidence such as acute myocardial infarction, stroke, pulmonary embolism, or other clinical indications of vascular occlusion. Patients who had documented histories of positive heparin-dependent antibody tests without current thrombocytopenia or heparin challenge (e.g., patients with latent disease) were also included if they required anticoagulation.

These studies did not include patients with documented unexplained aPTT > 200% of control at baseline, documented coagulation disorder or bleeding diathesis unrelated to HIT, a lumbar puncture within the past 7 days or a history of previous aneurysm, hemorrhagic stroke, or a thrombotic stroke within the past 6 months unrelated to HIT.

The initial dose of argatroban was 2 mcg/kg/min. Two hours after the start of the argatroban infusion, an aPTT level was obtained and dose adjustments were made (up to a maximum of 10 mcg/kg/min) to achieve a steady-state aPTT value that was 1.5 to 3 times the baseline value, not to exceed 100 seconds. Overall the mean aPTT level for HIT and HITTS patients during the Argatroban infusion increased from baseline values of 34 and 38 seconds, respectively, to 62.5 and 64.5 seconds, respectively.

The primary efficacy analysis was based on a comparison of event rates for a composite endpoint that included death (all causes), amputation (all causes) or new thrombosis during the treatment and follow-up period (study days 0 to 37). Secondary analyses included evaluation of the event rates for the components of the composite endpoint as well as time-to-event analyses.

In study 1, a total of 304 patients were enrolled as follows: active HIT (n=129), active HITTS (n=144), or latent disease (n=31). Among the 193 historical controls, 139 (72%) had active HIT, 46 (24%) had active HITTS, and 8 (4%) had latent disease. Within each group, those with active HIT and those with latent disease were analyzed together. Positive laboratory confirmation of HIT/HITTS by the heparin-induced platelet aggregation test or serotonin release assay was demonstrated in 174 of 304 (57%) argatroban-treated patients (i.e., in 80 with HIT or latent disease and 94 with HITTS) and in 149 of 193 (77%) historical controls (i.e., in 119 with HIT or latent disease and 30 with HITTS). The test results for the remainder of the patients and controls were either negative or not determined.

There was a significant improvement in the composite outcome in patients with HIT and HITTS treated with argatroban versus those in the historical control group (see Table 9). The components of the composite endpoint are shown in Table 9.

Table 9.
Efficacy Results of Study 1: Composite Endpointaand Individual Components, Ranked by
Severityb
 | HIT |  | HITTS |  | HIT/HITTS
Parameter, N (%) | Control n = 147 | Argatroban n = 160 | Control n = 46 | Argatroban n = 144 | Control n = 193 | Argatroban n = 304
Composite Endpoint | 57 (38.8) | 41 (25.6) | 26 (56.5) | 63 (43.8) | 83 (43) | 104 (34.2)
Individual Componentsb:
Parameter, N (%) | Control n = 147 | Argatroban n = 160 | Control n = 46 | Argatroban n = 144 | Control n = 193 | Argatroban n = 304
Death Amputation New Thrombosis | 32(21.8) 3(2) 22(15) | 27(16.9) 3(1.9) 11(6.9) | 13(28.3) 4(8.7) 9(19.6) | 26(18.1) 16(11.1) 21(14.6) | 45(23.3) 7(3.6) 31(16.1) | 53(17.4) 19(6.2) 32(10.5)
a) Death (all causes), amputation (all causes), or new thrombosis within 37-day study period.
b) Reported as the most severe outcome among the components of composite endpoint (severity ranking: death > amputation > new thrombosis); patients may have had multiple outcomes.

Time-to-event analyses showed significant improvements in the time-to-first event in patients with HIT or HITTS treated with argatroban versus those in the historical control group. The between-group differences in the proportion of patients who remained free of death, amputation, or new thrombosis were statistically significant in favor of argatroban by these analyses.

A time-to-event analysis for the composite endpoint is shown in Figure 3for patients with HIT and Figure 4for patients with HITTS.

Figure 3.
Time-to-First Event for the Composite Efficacy Endpoint: HIT Patients STUDY 1

Figure 4.
Time-to-First Event for the Composite Efficacy Endpoint: HITTS Patients STUDY 1

In Study 2, a total of 264 patients were enrolled as follows: HIT (n=125) or HITTS (n=139). There was a significant improvement in the composite efficacy outcome for argatroban-treated patients, versus the same historical control group from Study 1, among patients having HIT (25.6% vs. 38.8%), patients having HITTS (41% vs. 56.5%), and patients having either HIT or HITTS (33.7% vs. 43%). Time-to-event analyses showed significant improvements in the time-to-first event in patients with HIT or HITTS treated with argatroban versus those in the historical control group. The between-group differences in the proportion of patients who remained free of death, amputation, or new thrombosis were statistically significant in favor of argatroban.

Anticoagulant Effect:

In Study 1, the mean (± SE) dose of argatroban administered was 2 ± 0.1 mcg/kg/min in the HIT arm and 1.9 ± 0.1 mcg/kg/min in the HITTS arm. Seventy-six percent of patients with HIT and 81% of patients with HITTS achieved a target aPTT at least 1.5-fold greater than the baseline aPTT at the first assessment occurring on average at 4.6 hours (HIT) and 3.9 hours (HITTS) following initiation of argatroban therapy.

No enhancement of aPTT response was observed in subjects receiving repeated administration of argatroban.

Platelet Count Recovery:

In Study 1, 53% of patients with HIT and 58% of patients with HITTS, had a recovery of platelet count by Day 3. Platelet Count Recovery was defined as an increase in platelet count to > 100,000/μL or to at least 1.5-fold greater than the baseline count (platelet count at study initiation) by Day 3 of the study.

14.2 Percutaneous Coronary Intervention (PCI) Patients with or at Risk for HIT

In 3 similarly designed trials, argatroban was administered to 91 patients with current or previous clinical diagnosis of HIT or heparin-dependent antibodies, who underwent a total of 112 percutaneous coronary interventions (PCIs) including percutaneous transluminal coronary angioplasty (PTCA), coronary stent placement, or atherectomy. Among the 91 patients undergoing their first PCI with argatroban, notable ongoing or recent medical history included myocardial infarction (n = 35), unstable angina (n = 23), and chronic angina (n = 34). There were 33 females and 58 males. The average age was 67.6 years (median 70.7, range 44 to 86), and the average weight was 82.5 kg (median 81 kg, range 49 to 141).

Twenty-one of the 91 patients had a repeat PCI using argatroban an average of 150 days after their initial PCI. Seven of 91 patients received glycoprotein IIb/IIIa inhibitors. Safety and efficacy were assessed against historical control populations who had been anticoagulated with heparin.

All patients received oral aspirin (325 mg) 2 to 24 hours prior to the interventional procedure. After venous or arterial sheaths were in place, anticoagulation was initiated with a bolus of argatroban of 350 mcg/kg via a large-bore intravenous line or through the venous sheath over 3 to 5 minutes. Simultaneously, a maintenance infusion of 25 mcg/kg/min was initiated to achieve a therapeutic activated clotting time (ACT) of 300 to 450 seconds. If necessary to achieve this therapeutic range, the maintenance infusion dose was titrated (15 to 40 mcg/kg/min) and/or an additional bolus dose of 150 mcg/kg could be given. Each patient's ACT was checked 5 to 10 minutes following the bolus dose. The ACT was checked as clinically indicated. Arterial and venous sheaths were removed no sooner than 2 hours after discontinuation of argatroban and when the ACT was less than 160 seconds.

If a patient required anticoagulation after the procedure, argatroban could be continued, but at a lower infusion dose between 2.5 and 5 mcg/kg/min. An aPTT was drawn 2 hours after this dose reduction and the dose of argatroban then was adjusted as clinically indicated (not to exceed 10 mcg/kg/min), to reach an aPTT between 1.5 and 3 times baseline value (not to exceed 100 seconds).

In 92 of the 112 interventions (82%), the patient received the initial bolus of 350 mcg/kg and an initial infusion dose of 25 mcg/kg/min. The majority of patients did not require additional bolus dosing during the PCI procedure. The mean value for the initial ACT measurement after the start of dosing for all interventions was 379 sec (median 338 sec; 5thpercentile-95thpercentile 238 to 675 sec). The mean ACT value per intervention over all measurements taken during the procedure was 416 sec (median 390 sec; 5thpercentile-95thpercentile 261 to 698 sec). About 65% of patients had ACTs within the recommended range of 300 to 450 seconds throughout the procedure. The investigators did not achieve anticoagulation within the recommended range in about 23% of patients. However, in this small sample, patients with ACTs below 300 seconds did not have more coronary thrombotic events, and patients with ACTs over 450 seconds did not have higher bleeding rates.

Acute procedural success was defined as lack of death, emergent coronary artery bypass graft (CABG), or Q-wave myocardial infarction. Acute procedural success was reported in 98.2% of patients who underwent PCIs with argatroban anticoagulation compared with 94.3% of historical control patients anticoagulated with heparin (p = NS). Among the 112 interventions, 2 patients had emergency CABGs, 3 had repeat PTCAs, 4 had non-Q-wave myocardial infarctions, 3 had myocardial ischemia, 1 had an abrupt closure, and 1 had an impending closure (some patients may have experienced more than 1 event). No patients died.

16 HOW SUPPLIED/STORAGE AND HANDLING

Argatroban in Sodium Chloride Injection is supplied as a single-dose vial containing 50 mg argatroban in 50 mL of aqueous sodium chloride solution (1 mg/mL). The vial is sealed with a gray rubber stopper and a green aluminum flip-off seal.

NDC 16729-430-11 – Package containing one vial of Argatroban in Sodium Chloride injection (each vial contains 50 mg of argatroban).

NDC 16729-430-43 – Package containing 10 vials of Argatroban in Sodium Chloride injection (each vial contains 50 mg of argatroban).

Storage

Store the vials in original cartons at 20ºC to 25ºC (68ºF to 77°F) [see USP Controlled Room Temperature]: excursion permitted between 15°C to 30°C (59°F to 86°F). Do not refrigerate or freeze. Protect from light and store in carton. Do not use if solution is cloudy or contains a precipitate.

17 PATIENT COUNSELING INFORMATION

Inform patients of the risks associated with Argatroban in Sodium Chloride Injection as well as the plan for regular monitoring during administration of the drug.

Specifically inform patients to report:

- the use of any other products known to affect bleeding [see Drug Interactions (7)] .
- any medical history that may increase the risk for bleeding, including a history of severe hypertension; recent lumbar puncture or spinal anesthesia; major surgery, especially involving the brain, spinal cord, or eye; hematologic conditions associated with increased bleeding tendencies such as congenital or acquired bleeding disorders and gastrointestinal lesions such as ulcerations.
- any bleeding signs or symptoms [see Warnings and Precautions (5.1)] .
- the occurrence of any signs or symptoms of allergic reactions (e.g., airway reactions, skin reactions and vasodilation reactions). [see Adverse Reactions (6.1)] .

Manufactured For:
8041 Arco Corporate Drive,
Suite 200,
Raleigh, NC 27617,
USA.

Manufactured By:
Intas Pharmaceuticals Limited,
Plot No.: 457, 458,
Village – Matoda,
Bavla Road, Ta. - Sanand,
Dist.- Ahmedabad – 382 210.
India.
10 2465 1 6026245

Principal Display Panel - Carton Label

Principal Display Panel - Vial Label